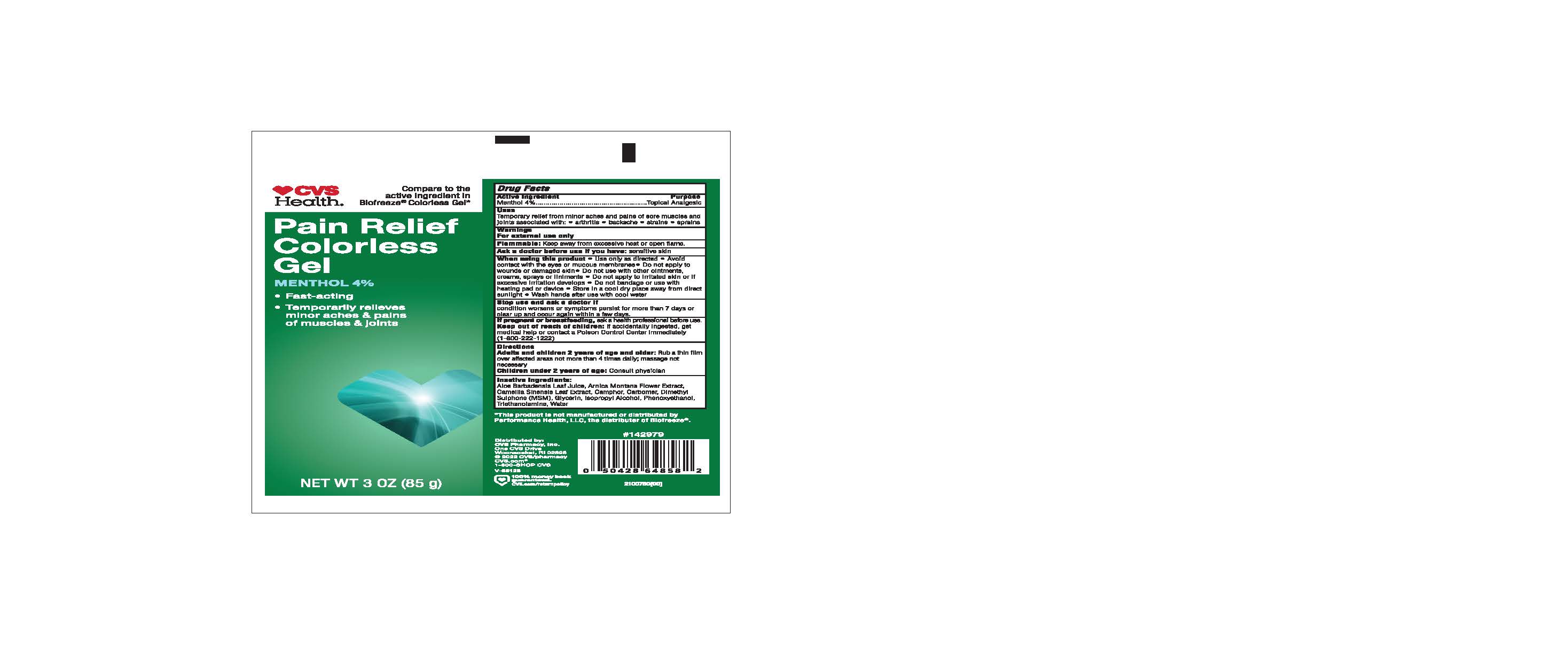 DRUG LABEL: CVS Pain Relief
NDC: 51316-997 | Form: GEL
Manufacturer: CVS
Category: otc | Type: HUMAN OTC DRUG LABEL
Date: 20241211

ACTIVE INGREDIENTS: MENTHOL 4 g/100 g
INACTIVE INGREDIENTS: GLYCERIN; DIMETHYL SULFONE; GREEN TEA LEAF; TROLAMINE; ISOPROPYL ALCOHOL; CARBOMER INTERPOLYMER TYPE A (ALLYL SUCROSE CROSSLINKED); ARNICA MONTANA; ALOE VERA LEAF; PHENOXYETHANOL; WATER; CAMPHOR (SYNTHETIC)

CVS Pain Relief Colorless Gel

ACTIVE INGREDIENT

Menthol 4%

PURPOSE

Topical Analgesic

INDICATIONS AND USAGE

Temporary relief from minor aches and pains of sore muscles and joints associated with:

arthritis

backache

strains

sprains

WARNINGS

For external use only

Flammable: Keep away from excessive heat or open flame

Ask a doctor before use if you have: sensitive skin

Stop use and ask a doctor if

condition worsens or symptoms persist for more than 7 days or clear up and occur again within a few days.

When using this product

Use only as directed

Avoid contact with eyes or mucous membranes

Do not apply to wounds or damaged skin

Do not use with other ointments, creams, sprays or liniments

Do not apply to irritated skin or if excessive irritation develops

Do not bandage or use with heating pad or device

Store in a cool dry place away from direct sunlight

Wash hands after use with cool water

PREGNANCY OR BREAST FEEDING

If pregnant or breastfeeding, ask a health professional before use

Keep out of reach of children: If accidentally ingested, get medical help or contact a poison Control immediately (1800-222-1222)

Directions

Adults and children 2 years of age and older: Rub a thin film over affected areas not more than daily: massage not necessary

Children under 2 years of age : Consult physician

INACTIVE INGREDIENT

Aloe Barbadensis Leaf Juice, Arnica Montana Flower Extract, Camellia Sinensis Leaf Extract, Camphor, Carbomer, Dimethyl Sulphone (MSM), Glycerin, Isopropyl Alcohol, Phenoxyethanol, Triethanolamine, Water